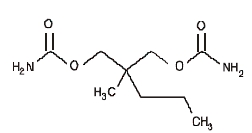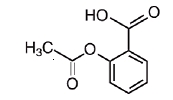 DRUG LABEL: Unknown
Manufacturer: Mikart, Inc.
Category: prescription | Type: Human prescription drug label
Date: 20080115

EQUAGESIC ® (meprobamate and aspirin tablets) CIV

Code 1019A00

Rev. 09/06

1-0047-1

Rx only

DESCRIPTION

Each tablet of Equagesic, for oral administration, contains 200 mg meprobamate and 325 mg aspirin. Chemically, meprobamate is 2-methyl-2-propyl-1,3- propanediol dicarbamate. Its molecular formula is C9H18N2O4 with a molecular weight of 218.25.

Chemically, aspirin is benzoic acid 2-(acetyloxy)-. Its molecular formula is C9H8O4 with a molecular weight of 180.16. It occurs as an odorless white, needle like crystalline or powdery substance. When exposed to moisture, aspirin hydrolyzes into salicylic and acetic acids, and gives off a vinegary odor. It is highly lipid soluble and slightly soluble in water. The structural formulas of meprobamate and aspirin are:

MEPROBAMATE
ASPIRIN

The inactive ingredients present are D&C Yellow 10, FD&C Red 3, FD&C Yellow 6, hydrogenated vegetable oil, magnesium stearate, microcrystalline cellulose, polacrilin potassium, and starch.

CLINICAL PHARMACOLOGY

Meprobamate is a carbamate derivative which has been shown (in animal and/or human studies) to have effects at multiple sites in the central nervous system, including the thalamus and limbic system. Aspirin is a nonnarcotic analgesic with antipyretic and anti-inflammatory properties.

INDICATIONS AND USAGE

As an adjunct in the short-term treatment of pain accompanied by tension and/or anxiety in patients with musculoskeletal disease. Clinical trials have demonstrated that in these situations relief of pain is somewhat greater than with aspirin alone. Equagesic is not intended for use longer than 10 days.

Contraindications

Usage in Pregnancy and Lactation

An increased risk of congenital malformations associated with the use of minor tranquilizers (meprobamate, chlordiazepoxide, and diazepam) during the first trimester of pregnancy has been suggested in several studies. Because use of these drugs is rarely a matter of urgency, their use during this period should almost always be avoided.

Because of the known effect of non-steroidal anti-inflammatory drugs (NSAIDs) on the fetal cardiovascular system (closure of the ductus arteriosus), use during the third trimester of pregnancy should be avoided. Salicylate products have also been associated with alterations in maternal and neonatal hemostasis mechanisms, decreased birth weight, and perinatal mortality. The possibility that a woman of childbearing potential may be pregnant at the time of institution of therapy should be considered. Patients should be advised that if they become pregnant during therapy or intend to become pregnant they should communicate with their physicians about the desirability of discontinuing the drug. Meprobamate passes the placental barrier. It is present both in umbilical-cord blood at or near maternal plasma levels and in breast milk of lactating mothers at concentrations two to four times that of maternal plasma. When use of meprobamate is contemplated in breast-feeding patients, the drug’s higher concentrations in breast milk as compared to maternal plasma levels should be considered.

Equagesic is contraindicated in patients with acute intermittent porphyria and in patients with allergic or idiosyncratic reactions to aspirin, meprobamate, or related compounds, such as carbromal, carisoprodol, mebutamate, nonsteroidal anti-inflammatory drug products, salicylates, or tybamate. Equagesic is also contraindicated in patients with the syndrome of asthma, rhinitis, and nasal polyps. The aspirin component of Equagesic may cause severe angioedema, bronchospasm (asthma), or urticaria. Reye’s syndrome: Aspirin should not be used in children or teenagers for viral infections, with or without fever, because of the risk of Reye’s syndrome with concomitant use of aspirin in certain viral illnesses.

WARNINGS

Equagesic should be prescribed cautiously and in small quantities to patients with suicidal tendencies.

Additive Effects: Since CNS-suppressant effects of meprobamate and alcohol or meprobamate and other psychotropic drugs may be additive, appropriate caution should be exercised with patients who take more than one of these agents simultaneously.

Alcohol Warning: Patients who consume three or more alcoholic drinks every day should be counseled about the bleeding risks involved with chronic, heavy alcohol use while taking aspirin.

Coagulation Abnormalities: Even low doses of aspirin can inhibit platelet function leading to an increase in bleeding time. This can adversely affect patients with inherited (hemophilia) or acquired (liver disease or vitamin K deficiency) bleeding disorders.

Gastrointestinal Side Effects (GI): GI side effects include gross GI bleeding, heartburn, nausea, stomach pain, and vomiting. Although minor upper GI symptoms, such as dyspepsia, are common and can occur anytime during therapy, physicians should remain alert for signs of ulceration and bleeding, even in the absence of previous GI symptoms. Physicians should inform patients about the signs and symptoms of GI side effects and what steps to take if they occur.

Peptic Ulcer Disease: Patients with a history of active peptic ulcer disease should avoid using aspirin, which can cause gastric mucosal irritation and bleeding.

Potentially Hazardous Tasks

Patients should be warned that meprobamate may impair the mental and/or physical abilities required for performance of potentially hazardous tasks, such as driving a motor vehicle or operating machinery. Such tasks should be avoided while taking this product.

PRECAUTIONS

General

Equagesic should be prescribed with caution in certain special-risk populations, such as elderly or debilitated patients and those with acute abdominal conditions, Addison’s disease, coagulation disorders, elevated intracranial pressure, head injuries, hypothyroidism, impairment of liver or kidney function, prostatic hypertrophy, or urethral stricture. Meprobamate is metabolized in the liver and excreted by the kidney. To avoid its excess accumulation, caution should be exercised in the administration to patients with compromised liver or kidney function. Meprobamate occasionally may precipitate seizures in epileptic patients.

Information for Patients

Patients should be informed that Equagesic contains aspirin and should not be taken by patients with an aspirin allergy.

Patients with a predisposition for gastrointestinal bleeding should be cautioned that concomitant use of medications containing aspirin and/or alcohol may have an additive effect in this regard.

Drug Interactions

Angiotensin Converting Enzyme (ACE) Inhibitors: The hyponatremic and hypotensive effects of ACE inhibitors may be diminished by the concomitant administration of aspirin due to its indirect effect on the reninangiotensin conversion pathway.

Acetazolamide: Concurrent use of aspirin and acetazolamide can lead to high serum concentrations of acetazolamide (and toxicity) due to competition at the renal tubule for secretion.

Alcohol, General Anesthetics, Narcotic Analgesics, Sedative Hypnotics, Tranquilizers such as Chlordiazepoxide, or Other CNS Depressants: The effects of these substances may be enhanced, causing increased CNS depression.

Anticoagulant Therapy (Heparin and Warfarin): Patients on anticoagulation therapy are at increased risk for bleeding because of drug-drug interactions and the effect on platelets. Aspirin can displace warfarin from protein binding sites, leading to prolongation of both the prothrombin time and the bleeding time. Aspirin can increase the anticoagulant activity of heparin, increasing bleeding risk.

Anticonvulsants: Salicylates can displace protein-bound phenytoin and valproic acid, leading to a decrease in the total concentration of phenytoin and an increase in serum valproic acid levels.

Beta Blockers: The hypotensive effects of beta blockers may be diminished by the concomitant administration of aspirin due to inhibition of renal prostaglandins, leading to decreased renal blood flow and salt and fluid retention.

Corticosteroids: In patients receiving concomitant corticosteroids and chronic use of medications containing aspirin, withdrawal of corticosteroids may result in salicylism because corticosteroids enhance renal clearance of salicylates and their withdrawal is followed by return to normal rates of renal clearance.

Diuretics: The effectiveness of diuretics in patients with underlying renal or cardiovascular disease may be diminished by the concomitant administration of aspirin due to inhibition of renal prostaglandins, leading to decreased renal blood flow and salt and fluid retention.

6-Mercaptopurine and Methotrexate: Bone marrow toxicity and blood dyscrasia may result from displacing these drugs from secondary binding sites, and in the case of methotrexate, also reducing its excretion.

Nonsteroidal Anti-Inflammatory Drugs (NSAIDs): The concurrent use of aspirin with other NSAIDs should be avoided because this may increase bleeding or lead to decreased renal function.

Oral Hypoglycemics: Moderate doses of aspirin may increase the effectiveness of oral hypoglycemic drugs, leading to hypoglycemia.

Uricosuric Agents (Probenicid and Sulfinpyrazone): Salicylates antagonize the uricosuric action, reducing their effectiveness in the treatment of gout. Aspirin competes with these agents for protein binding sites.

Laboratory Test Interactions

Aspirin may interfere with the following laboratory determinations in blood: blood urea nitrogen, cholesterol, elevated hepatic enzymes including aspartate aminotransferase (AST), fasting blood glucose, hyperkalemia, prolonged bleeding time, protein, prothrombin time, serum amylase, serum creatinine, and uric acid. Aspirin may interfere with the following laboratory determinations in urine: 5-hydroxyindoleacetic acid, diacetic acid, Gerhardt ketone, glucose, proteinuria, uric acid, spectrophotometric detection of barbiturates, and vanillylmandelic acid (VMA).

Carcinogenesis, Mutagenesis Impairment of Fertility

Administration of aspirin for 68 weeks at 0.5 percent in the feed of rats was not carcinogenic. In the Ames Salmonella assay, aspirin was not mutagenic; however, aspirin did induce chromosome aberrations in cultured human fibroblasts.

Pregnancy: Teratogenic Effects. Pregnancy Category X.

See Contraindications

Labor and Delivery

Aspirin should be avoided during the third trimester of pregnancy and during labor and delivery because it can result in excessive blood loss at delivery. Prolonged gestation and prolonged labor due to prostaglandin inhibition have been reported.

Nursing Mothers

Nursing mothers should avoid using aspirin because salicylate is excreted in breast milk. Use of high doses may lead to rashes, platelet abnormalities, and bleeding in nursing infants. Because of the potential for serious adverse reactions in nursing infants, a decision should be made whether to discontinue nursing or to discontinue the drug, taking into account the importance of the drug to the mother (See also Contraindications).

Pediatric Use

Safety and effectiveness have not been established for pediatric patients under the age of 12 years (See Contraindications).

Geriatric Use

Clinical studies of meprobamate with aspirin did not include sufficient numbers of subjects aged 65 and over to determine whether they respond differently from younger subjects. In general, dose selection for an elderly patient should be cautious, usually starting at the low end of the dosing range, reflecting the greater frequency of decreased hepatic, renal, or cardiac function, and of concomitant disease or other drug therapy.

Adverse Reactions

Body as a Whole

Fever, hypothermia, thirst.

Allergic or Idiosyncratic

Severe hypersensitivity reactions, including anaphylaxis, angioneurotic edema, anuria, asthma, bronchospasm, bullous dermatitis, chills, erythema multiforme, exfoliative erythroderma, laryngeal edema, oliguria, proctitis, purpura, Stevens-Johnson syndrome, stomatitis, and urticaria. Milder reactions are characterized by an itchy, erythematous maculopapular, or urticarial rash which may be generalized or confined to the groin. Other reactions have included acute nonthrombocytopenic purpura, adenopathy, cross-sensitivity between meprobamate/ mebutamate and meprobamate/carbromal, ecchymoses, eosinophilia, fixed-drug eruption with cross-reaction to carisoprodol, leukopenia, peripheral edema, and petechiae.

Cardiovascular

Various forms of arrhythmia, hypotension, palpitation, syncope, tachycardia, and transient ECG changes.

Central Nervous System

Agitation, ataxia, cerebral edema, coma, confusion, dizziness, drowsiness, dysphoria, euphoria, fast EEG activity, headache, impairment of visual accommodation, lethargy, overstimulation, paradoxical excitement, paresthesias, sedation, slurred speech, subdural or intracranial hemorrhage, seizures, vertigo, and weakness.

Fluid and Electrolyte

Dehydration, hyperkalemia, metabolic acidosis, and respiratory alkalosis.

Gastrointestinal

Abdominal pain, constipation, diarrhea, dyspepsia, epigastric discomfort, gastric distress, gastrointestinal bleeding, heartburn, hepatitis, nausea, pancreatitis, Reye’s syndrome, transient elevations of hepatic enzymes, ulceration and perforation, and vomiting.

Hematologic (see also “Allergic or Idiosyncratic”)

Agranulocytosis and aplastic anemia have been reported, although no causal relationship has been established, coagulopathy, disseminated intravascular coagulation, exacerbation of porphyric symptoms, hemolytic anemia, iron deficiency anemia, occult blood loss, prolongation of the prothrombin time, thrombocytopenia, and thrombocytopenic purpura.

Musculoskeletal

Rhabdomyolysis

Metabolism

Hyperglycemia and hypoglycemia

Reproductive

Prolonged pregnancy and labor, stillbirths, lower birth weight infants, and antepartum and postpartum bleeding.

Respiratory

Acute airway obstruction, hyperpnea, pulmonary edema, and tachypnea.

Special Senses

Hearing loss and tinnitus.

Urogenital

Interstitial nephritis, papillary necrosis, proteinuria, and renal insufficiency and failure.

Drug Abuse and Dependence

Physical dependence, psychological dependence, and abuse have occurred. Chronic intoxication from prolonged ingestion of, usually, greater-than-recommended doses is manifested by ataxia, slurred speech, and vertigo. Therefore, careful supervision of dose and amounts prescribed is advised, as well as avoidance of prolonged administration, especially for alcoholics and other patients with a known propensity for taking excessive quantities of drugs. Sudden withdrawal of the drug after prolonged and excessive use may precipitate recurrence of preexisting symptoms, such as anorexia, anxiety, or insomnia, or withdrawal reactions, such as ataxia, confusional states, hallucinosis, muscle twitching, tremors, vomiting, and, rarely, convulsive seizures. Such seizures are more likely to occur in persons with central nervous system damage or preexistent or latent convulsive disorders. Onset of withdrawal symptoms occurs usually within 12 to 48 hours after discontinuation of meprobamate; symptoms usually cease within the next 12- to 48-hour period. When excessive dosage has continued for weeks or months, dosage should be reduced gradually over a period of 1 to 2 weeks rather than abruptly stopped. Alternatively, a long-acting barbiturate may be substituted, then gradually withdrawn.

Overdosage

Treatment of overdose with Equagesic is essentially symptomatic and supportive. In cases where excessive doses of Equagesic have been taken, sleep ensues rapidly and blood pressure, pulse, and respiratory rates are reduced to basal levels. Any drug remaining in the stomach should be removed and symptomatic treatment given. After emesis and/or lavage, activated charcoal may reduce absorption of both aspirin and meprobamate. Should respiration or blood pressure become compromised, respiratory assistance, central nervous system stimulants, and pressor agents should be administered cautiously as indicated. Diuresis, osmotic (mannitol) diuresis, peritoneal dialysis, and hemodialysis have been used successfully in removing both aspirin and meprobamate. Alkalinization of the urine increases the excretion of salicylates. Careful monitoring of urinary output is necessary, and caution should be taken to avoid overhydration. Relapse and death, after initial recovery, have been attributed to incomplete gastric emptying and delayed absorption. Salicylate toxicity may result from acute ingestion (overdose) or chronic intoxication. Signs and symptoms include abdominal pain, acid-base disturbances with development of metabolic acidosis, convulsions, delirium, hyperpnea, hyperthermia, hypoprothrombinemia, restlessness, Tinnitus (ringing in the ears), and vomiting. The early signs of salicylic overdose (salicylism), including tinnitus, occur at plasma concentrations approaching 200 μg/mL. Plasma concentrations of aspirin above 300 μg/mL are clearly toxic. Severe toxic effects are associated with levels above 400 μg/mL. A single lethal dose of aspirin in adults is not known with certainty but death may be expected at 30 g. For real or suspected overdose, a Poison Control Center should be contacted immediately. Careful medical management is essential. In acute aspirin overdose, severe acid-base and electrolyte disturbances may occur and are complicated by hyperthermia and dehydration. Respiratory alkalosis occurs early while hyperventilation is present, but is quickly followed by metabolic acidosis. Treatment of aspirin overdose consists primarily of supporting vital functions, increasing salicylate elimination, and correcting the acid-base disturbance. Gastric emptying and/or lavage is recommended as soon as possible after ingestion, even if the patient has vomited spontaneously. After lavage and/or emesis administration of activated charcoal, as a slurry, is beneficial, if less than 3 hours have passed since ingestion. Charcoal adsorption should not be employed prior to emesis and lavage.

Severity of aspirin intoxication is determined by measuring the blood salicylate level. Acid-base status should be closely followed with serial blood gas and serum pH measurements. Fluid and electrolyte balance should also be maintained. In severe cases, hyperthermia and hypovolemia are the immediate threats to life. Children should be sponged with tepid water. Replacement fluid should be administered intravenously and augmented with correction of acidosis. Plasma electrolytes and pH should be monitored to promote alkaline diuresis of salicylate if renal function is normal. Infusion of glucose may be required to control hypoglycemia.

Hemodialysis and peritoneal dialysis can be performed to reduce the body drug content. In patients with renal insufficiency or in cases of life-threatening intoxication, dialysis is usually required. Exchange transfusion may be indicated in infants and young children. Suicidal attempts with meprobamate have resulted in ataxia, coma, drowsiness, lethargy, shock, stupor, and respiratory and vasomotor collapse. Some suicidal attempts have been fatal. The following data have been reported in the literature and from other sources. These data are not expected to correlate with each case (considering factors such as individual susceptibility and length of time from ingestion to treatment) but represent the usual ranges reported. Acute simple overdose (meprobamate alone): Death has been reported with ingestion of as little as 12 grams meprobamate and survival with as much as 40 grams.

BLOOD LEVELS

0.5 to 2 mg percent represents the usual blood-level range of meprobamate after therapeutic doses. 3 to 10 mg percent usually corresponds to findings of mild to moderate symptoms of overdosage, such as stupor or light coma. 10 to 20 mg percent usually corresponds to deeper coma, requiring more intensive treatment. Some fatalities occur. At levels greater than 20 mg percent, more fatalities than survivals can be expected. Acute combined overdose (meprobamate with other CNS psychotropic drugs or alcohol): Since effects can be additive, a history of ingestion of a low dose of meprobamate plus any of these compounds (or of a relatively low blood or tissue level) cannot be used as a prognostic indicator.

Dosage and Administration

The usual dosage of Equagesic is one or two tablets, each tablet containing meprobamate, 200 mg, and aspirin, 325 mg, orally 3 to 4 times daily as needed for the relief of pain when tension or anxiety is present. Equagesic is not recommended for patients 12 years of age and under.

How Supplied

Equagesic® (meprobamate and aspirin tablets) Tablets, 200 mg meprobamate and 325 mg aspirin, are available as follows: NDC 10551-091-10, pink and yellow, double-layer, round, scored tablet marked “LP” and “91”, in bottles of 100 tablets.

Store at controlled room temperature, 20°-25°C (68°-77°F).

Protect from moisture.

Keep tightly closed.

Protect from light.

Dispense in light-resistant, tight container.

Manufactured for:

Leitner Pharmaceuticals™, LLC

Bristol, TN 37620

www.leitnerpharma.com

Manufactured by:

Mikart, Inc.

Atlanta, GA 30318

1019A00

09/06

1-0047-1